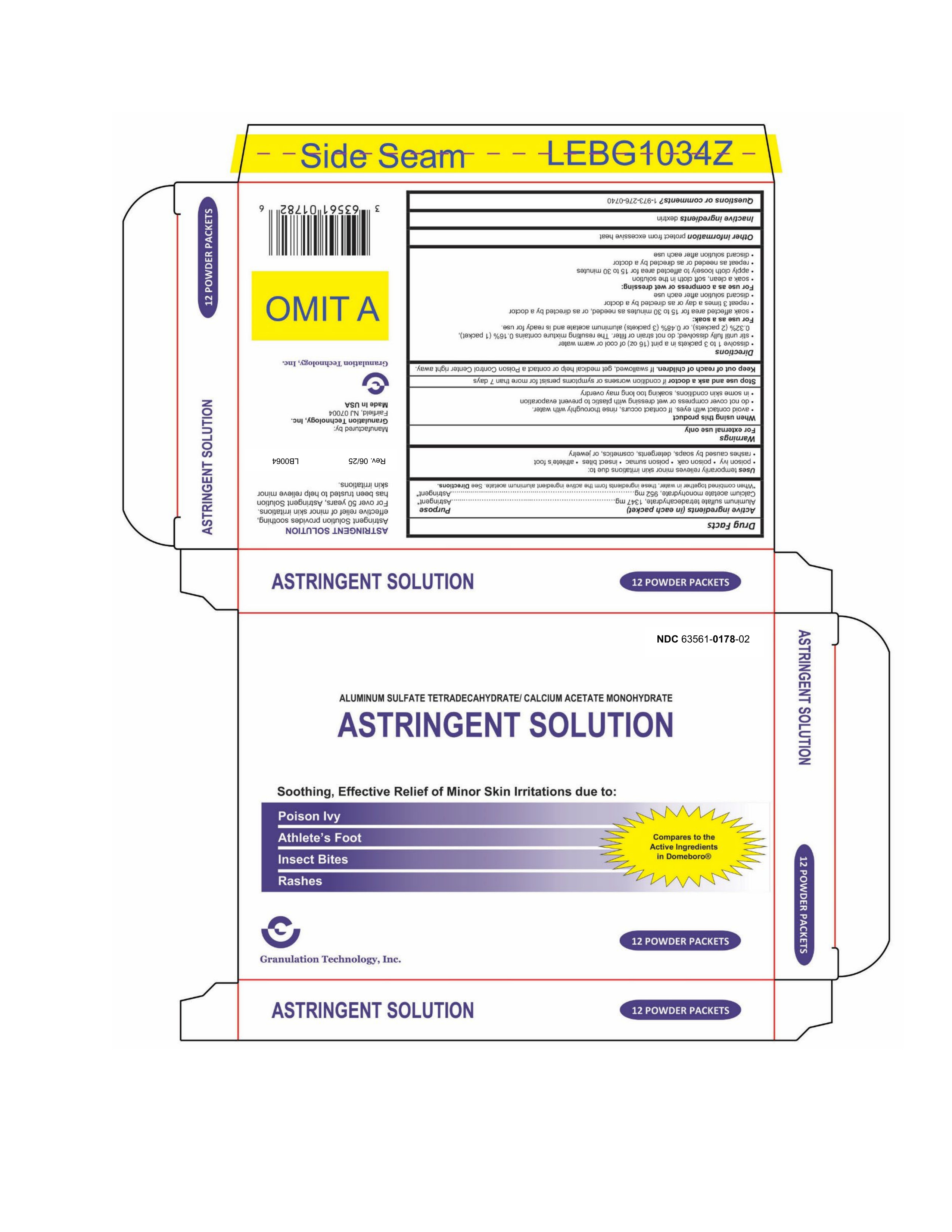 DRUG LABEL: Astringent
NDC: 63561-0178 | Form: POWDER, FOR SOLUTION
Manufacturer: Granulation Technology, Inc.
Category: otc | Type: HUMAN OTC DRUG LABEL
Date: 20250612

ACTIVE INGREDIENTS: CALCIUM ACETATE MONOHYDRATE 952 mg/2299 mg; ALUMINUM SULFATE TETRADECAHYDRATE 1347 mg/2299 mg
INACTIVE INGREDIENTS: MALTODEXTRIN

Astringent Solution

Drug Facts

ACTIVE INGREDIENT

Active ingredients (in each packet) | Purpose
Aluminum sulfate tetradecahydrate, 1347 mg | Astringent [When combined together in water, these ingredients form the active ingredient aluminum acetate. See Directions.]
Calcium acetate monohydrate, 952 mg | Astringent

Uses

Temporarily relieves minor skin irritations due to:

- Poison ivy
- Poison oak
- Poison sumac
- Insect bites
- Athlete's foot
- Rashes caused by soaps, detergents, cosmetics, or jewelry

Warnings

For external use only

When using this product

- Avoid contact with eyes. If contact occurs, rinse thoroughly with water.
- Do not cover compress or wet dressing with plastic to prevent evaporation
- In some skin conditions, soaking too long may overdry

Stop use and ask a doctor if condition worsens or symptoms persist for more than 7 days

Keep out of reach of children. If swallowed, get medical help or contact a Poison Control Center right away.

Directions

- Dissolve 1 to 3 packets in a pint (16 oz) of cool or warm water
- stir until fully dissolved; do not strain or filter. The resulting mixture contains 0.16% (1 packet), 0.32% (2 packets), or 0.48% (3 packets) aluminum acetate and is ready for use.

For use as a soak:

- Soak affected area for 15 to 30 minutes as needed, or as directed by a doctor
- Repeat 3 times a day or as directed by a doctor
- Discard solution after each use

For use as a compress or wet dressing:

- Soak a clean, soft cloth in the solution
- Apply cloth loosely to affected area for 15 to 30 minutes
- Repeat as needed or as directed by a doctor
- Discard solution after each use

Other information

Protect from excessive heat

Inactive ingredients

Dextrin

Questions or comments?

1-973-276-0740

Manufactured by:
Granulation Technology, Inc.
Fairfield, NJ 07004
Made In USA

PRINCIPAL DISPLAY PANEL - 2299 mg Packet Carton

NDC 63561-0178-02

ALUMINUM SULFATE TETRADECAHYDRATE / CALCIUM ACETATE MONOHYDRATE
ASTRINGENT SOLUTION

Soothing, Effective Relief of Minor Skin Irritations due to:

Poison Ivy
Athlete's Foot
Insect Bites
Rashes

Compares to the Active Ingredients in Domeboro®

Granulation Technology, Inc.

12 POWDER PACKETS